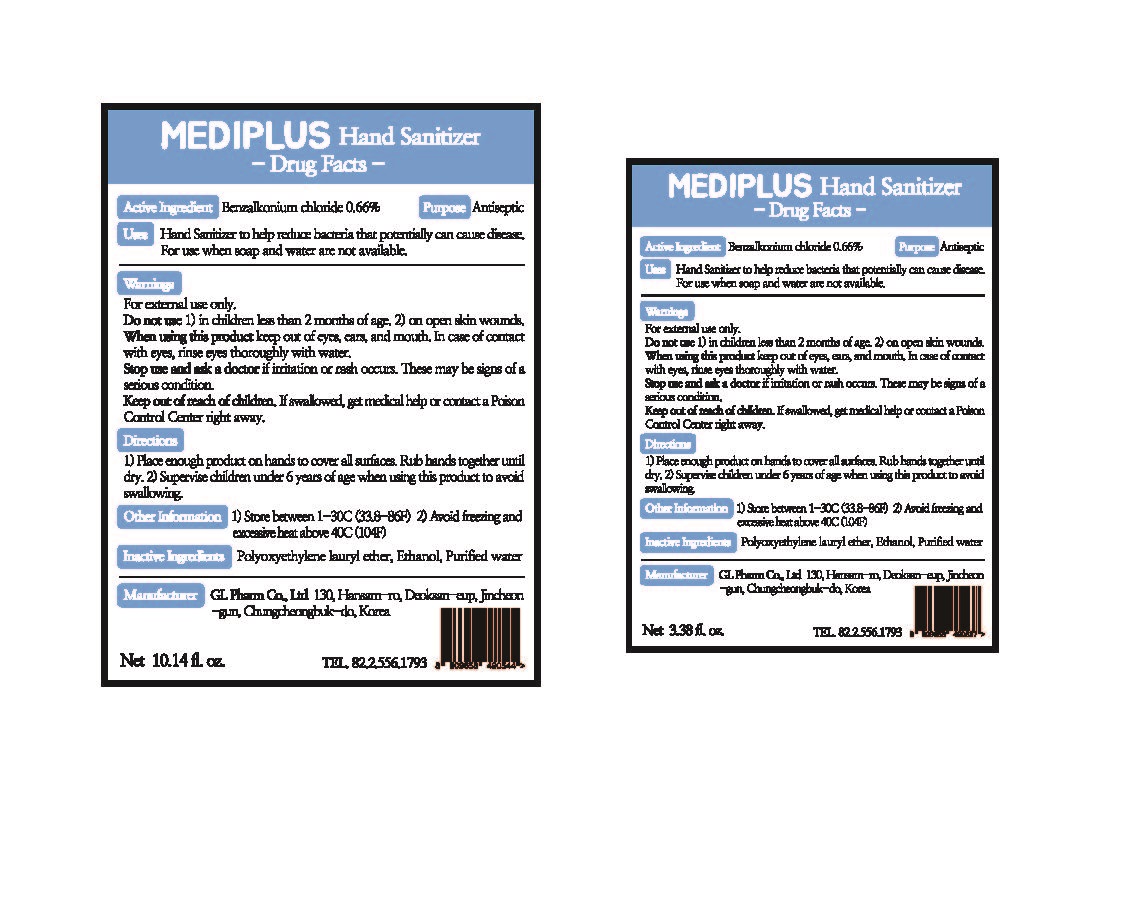 DRUG LABEL: MEDIPLUS Hand Sanitizer
NDC: 74713-0001 | Form: LIQUID
Manufacturer: GL Pharm Co Ltd
Category: otc | Type: HUMAN OTC DRUG LABEL
Date: 20200409

ACTIVE INGREDIENTS: BENZALKONIUM CHLORIDE 0.66 g/100 mL
INACTIVE INGREDIENTS: WATER; ALCOHOL

Drug Facts

ACTIVE INGREDIENT

benzaklonium chloride 0.66%

INACTIVE INGREDIENT

polyoxyethylene lauryl ether, ethanol, purified water

PURPOSE

hand sanitizer

KEEP OUT OF REACH OF THE CHILDREN

INDICATIONS AND USAGE

Apply to clean, dry hands. Apply sufficient amount to thoroughly wet all surfaces of hands and fingers. Rub onto hands until dry.

Supervise children in the use of this product.

WARNINGS

■ Flammable. Keep away from fire or flame.

■ For external use only.

■ Do not use in eyes.

■ lf swallowed, get medical help promptly.

■ Stop use, ask doctor lf irritation occurs.

■ Keep out of reach of children.

DOSAGE AND ADMINISTRATION

for external use only